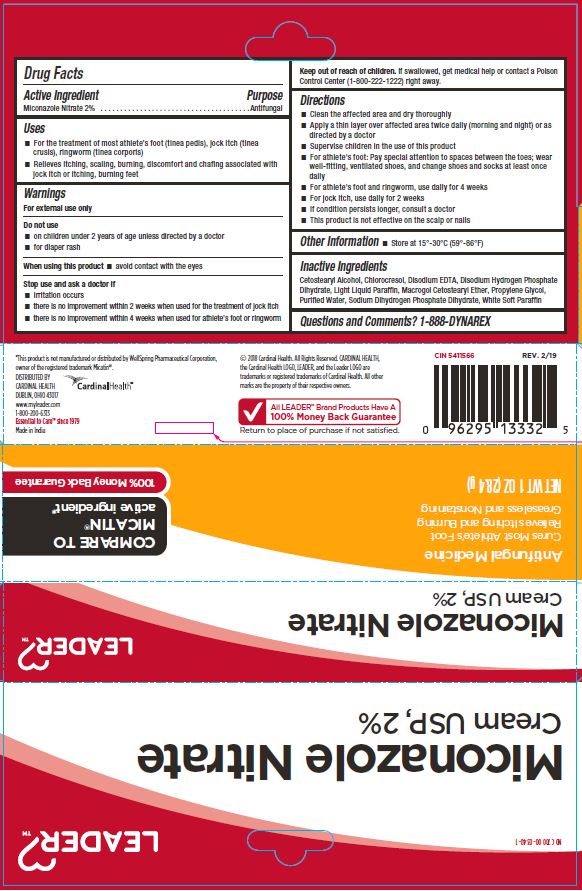 DRUG LABEL: Miconazole Nitrate Cream USP, 2%
NDC: 70000-0340 | Form: CREAM
Manufacturer: Cardinal Health
Category: otc | Type: HUMAN OTC DRUG LABEL
Date: 20251125

ACTIVE INGREDIENTS: MICONAZOLE NITRATE 2 g/100 g
INACTIVE INGREDIENTS: PETROLATUM; SODIUM PHOSPHATE DIBASIC DIHYDRATE; SODIUM PHOSPHATE, MONOBASIC, DIHYDRATE; EDETATE DISODIUM ANHYDROUS; CETEARETH-12; CETOSTEARYL ALCOHOL; CHLOROCRESOL; LIGHT MINERAL OIL; PROPYLENE GLYCOL; WATER

CR-1232

Active Ingredient

Miconazole Nitrate 2%

Purpose

Antifungal

Uses

- For the treatment of most athlete's foot, tinea pedis, jock itch, tinea crusis, ringworm, tinea corporis
- Relieves itching, scaling, burning, discomfort and chafing associated with jock itch or itching, burning feet

Warnings

For external use only

Do not use

- on children under 2 years of age unless directed by a doctor
- for diaper rash

When using this product

avoid contact with the eyes

Stop use and ask a doctor if

- irritation occurs
- there is no improvement within 2 weeks when used for the treatment of jock itch
- there is no improvement within 4 weeks when used for athlete's foot or ringworm

KEEP OUT OF REACH OF CHILDREN

If swallowed, get medical help or contact a Poison Control Center (1800-222-1222) right away.

Directions

- Clean the affected area and dry thoroughly
- Apply a thin layer over affected area twice daily (morning and night) or as directed by a doctor
- Supervise children in the use of this product
- For athlete's foot: Pay special attention to spaces between the toes; wear well-fitting, ventilated shoes, and change shoes and socks at least once daily
- For athlete's foot and ringworm, use daily for 4 weeks
- For jock itch, use daily for 2 weeks
- If condition persists longer, consult a doctor
- This product is not effective on the scalp or nails

Other Information

Store at 15° -30°C (59° -86°F)

Inactive Ingredients

Cetostearyl Alcohol, Chlorocresol, Disodium EDTA, Disodium Hydrogen Phosphate Dihydrate, Light Liquid Paraffin, Macrogol Cetostearyl Ether, Propylene Glycol, Purified Water, Sodium Dihydrogen Phosphate Dihydrate, White Soft Paraffin

Questions

1-888-DYNAREX